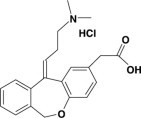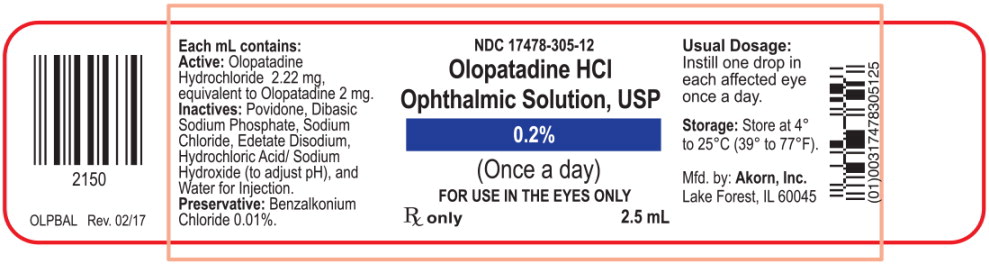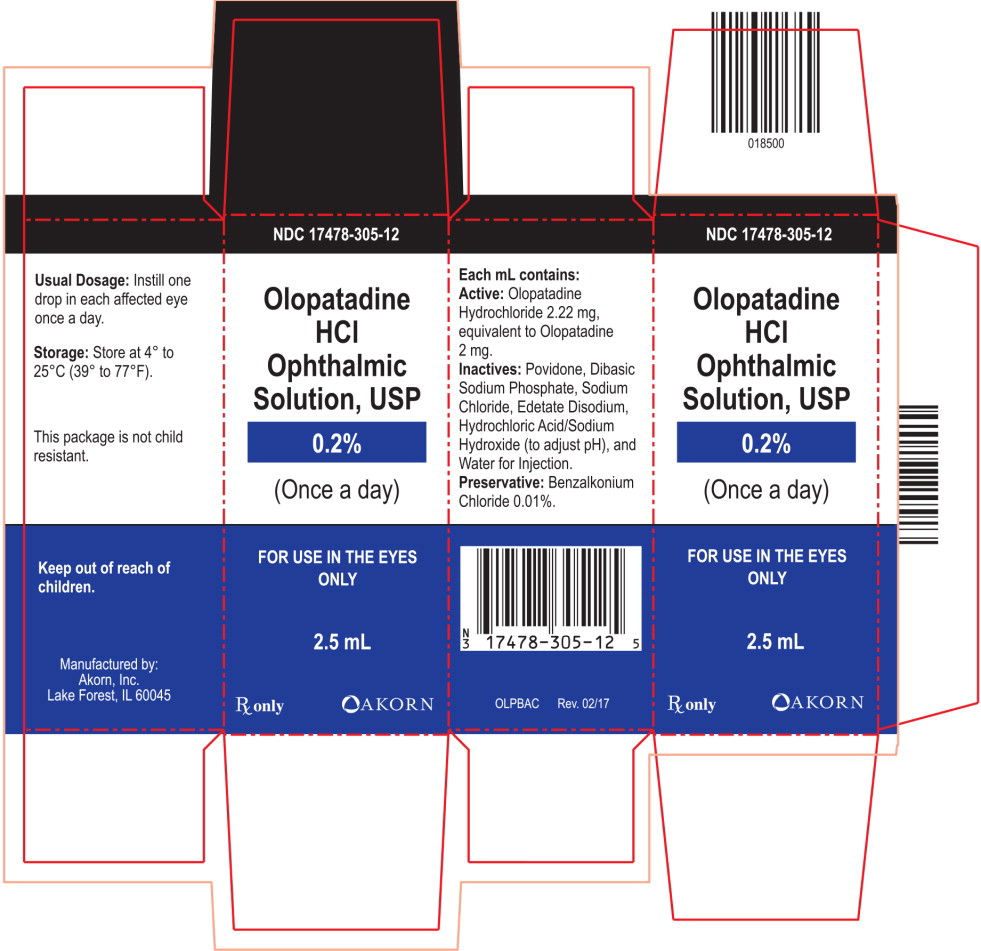 DRUG LABEL: Olopatadine
NDC: 17478-305 | Form: SOLUTION/ DROPS
Manufacturer: Akorn
Category: prescription | Type: HUMAN PRESCRIPTION DRUG LABEL
Date: 20220203

ACTIVE INGREDIENTS: Olopatadine Hydrochloride 2 mg/1 mL
INACTIVE INGREDIENTS: Povidone, Unspecified; Sodium Phosphate, Dibasic, Unspecified Form; Sodium Chloride; Edetate Disodium; Hydrochloric Acid; Sodium Hydroxide; Water; Benzalkonium Chloride

HIGHLIGHTS OF PRESCRIBING INFORMATION

These highlights do not include all the information needed to use Olopatadine Hydrochloride Ophthalmic Solution USP, 0.2% safely and effectively. See full prescribing information for Olopatadine Hydrochloride Ophthalmic Solution USP, 0.2%.
Olopatadine Hydrochloride Ophthalmic Solution USP, 0.2%
Initial U.S. Approval: 1996

1 INDICATIONS AND USAGE

Olopatadine Hydrochloride Ophthalmic Solution USP, 0.2% is a mast cell stabilizer indicated for the treatment of ocular itching associated with allergic conjunctivitis. (1)

2 DOSAGE AND ADMINISTRATION

The recommended dose is one drop in each affected eye once a day. (2)

3 DOSAGE FORMS AND STRENGTHS

Ophthalmic solution 0.2%: each mL contains 2.22 mg of olopatadine hydrochloride. (3)

5 WARNINGS AND PRECAUTIONS

For topical ocular use only. Not for injection or oral use. (5.1)

6 ADVERSE REACTIONS

Symptoms similar to cold syndrome and pharyngitis were reported at an incidence of approximately 10%. (6)

To report SUSPECTED ADVERSE REACTIONS, contact Akorn, Inc. at 1-800-932-5676 or FDA at 1-800-FDA-1088 or www.fda.gov/medwatch.

FULL PRESCRIBING INFORMATION

1 INDICATIONS AND USAGE

Olopatadine Hydrochloride Ophthalmic Solution USP, 0.2% is indicated for the treatment of ocular itching associated with allergic conjunctivitis.

2 DOSAGE AND ADMINISTRATION

The recommended dose is one drop in each affected eye once a day.

3 DOSAGE FORMS AND STRENGTHS

Ophthalmic solution 0.2%: each mL contains 2.22 mg of olopatadine hydrochloride.

4 CONTRAINDICATIONS

None.

5 WARNINGS AND PRECAUTIONS

5.1 For topical ocular use only

Not for injection or oral use.

5.2 Contamination of Tip and Solution

As with any eye drop, to prevent contaminating the dropper tip and solution, care should be taken not to touch the eyelids or surrounding areas with the dropper tip of the bottle. Keep bottle tightly closed when not in use.

5.3 Contact Lens Use

Patients should be advised not to wear a contact lens if their eye is red.

Olopatadine Hydrochloride Ophthalmic Solution USP, 0.2% should not be used to treat contact lens related irritation.

The preservative in Olopatadine Hydrochloride Ophthalmic Solution USP, 0.2%, benzalkonium chloride, may be absorbed by soft contact lenses. Patients who wear soft contact lenses and whose eyes are not red, should be instructed to wait at least ten minutes after instilling Olopatadine Hydrochloride Ophthalmic Solution USP, 0.2% before they insert their contact lenses.

6 ADVERSE REACTIONS

Symptoms similar to cold syndrome and pharyngitis were reported at an incidence of approximately 10%.

The following adverse experiences have been reported in 5% or less of patients:

Ocular: blurred vision, burning or stinging, conjunctivitis, dry eye, foreign body sensation, hyperemia, hypersensitivity, keratitis, lid edema, pain and ocular pruritus.

Non-ocular: asthenia, back pain, flu syndrome, headache, increased cough, infection, nausea, rhinitis, sinusitis and taste perversion.

Some of these events were similar to the underlying disease being studied.

8 USE IN SPECIFIC POPULATIONS

8.1 Pregnancy

Teratogenic effects: Pregnancy Category C

Olopatadine was found not to be teratogenic in rats and rabbits. However, rats treated at 600 mg/kg/day, or 150,000 times the MROHD and rabbits treated at 400 mg/kg/day, or approximately 100,000 times the MROHD, during organogenesis showed a decrease in live fetuses. In addition, rats treated with 600 mg/kg/day of olopatadine during organogenesis showed a decrease in fetal weight. Further, rats treated with 600 mg/kg/day of olopatadine during late gestation through the lactation period showed a decrease in neonatal survival and body weight. There are, however, no adequate and well-controlled studies in pregnant women. Because animal studies are not always predictive of human responses, this drug should be used in pregnant women only if the potential benefit to the mother justifies the potential risk to the embryo or fetus.

8.3 Nursing Mothers

Olopatadine has been identified in the milk of nursing rats following oral administration. It is not known whether topical ocular administration could result in sufficient systemic absorption to produce detectable quantities in the human breast milk. Nevertheless, caution should be exercised when Olopatadine Hydrochloride Ophthalmic Solution USP, 0.2% is administered to a nursing mother.

8.4 Pediatric Use

Safety and effectiveness in pediatric patients below the age of 2 years have not been established.

8.5 Geriatric Use

No overall differences in safety and effectiveness have been observed between elderly and younger patients.

11 DESCRIPTION

Olopatadine Hydrochloride Ophthalmic Solution USP, 0.2% is a sterile ophthalmic solution containing olopatadine for topical administration to the eyes. Olopatadine hydrochloride is a white, crystalline, water-soluble powder with a molecular weight of 373.88 and a molecular formula of C21H23NO3 • HCl. The chemical structure is presented below:

Chemical Name: 11-[(Z)-3-(Dimethylamino) propylidene]-6-11-dihydrodibenz[b,e] oxepin-2- acetic acid, hydrochloride

Each mL of Olopatadine Hydrochloride Ophthalmic Solution USP, 0.2% contains: Active: 2.22 mg Olopatadine Hydrochloride equivalent to 2 mg Olopatadine. Inactives: Povidone; Dibasic Sodium Phosphate; Sodium Chloride; Edetate Disodium; Benzalkonium Chloride 0.01% (Preservative); Hydrochloric Acid/Sodium Hydroxide (adjust pH); and Water for Injection.

It has a pH of approximately 7 and an osmolality of approximately 300 mOsm/kg.

12 CLINICAL PHARMACOLOGY

12.1 Mechanism of Action

Olopatadine is a mast cell stabilizer and a histamine H1 antagonist. Decreased chemotaxis and inhibition of eosinophil activation has also been demonstrated.

12.3 Pharmacokinetics

Systemic bioavailability data upon topical ocular administration of Olopatadine Hydrochloride Ophthalmic Solution USP, 0.2% solution are not available. Following topical ocular administration of olopatadine 0.15% ophthalmic solution in man, olopatadine was shown to have a low systemic exposure. Two studies in normal volunteers (totaling 24 subjects) dosed bilaterally with olopatadine 0.15% ophthalmic solution once every 12 hours for 2 weeks demonstrated plasma concentrations to be generally below the quantitation limit of the assay (< 0.5 ng/mL). Samples in which olopatadine was quantifiable were typically found within 2 hours of dosing and ranged from 0.5 to 1.3 ng/mL. The elimination half-life in plasma following oral dosing was 8 to 12 hours, and elimination was predominantly through renal excretion. Approximately 60 to 70% of the dose was recovered in the urine as parent drug. Two metabolites, the mono-desmethyl and the N-oxide, were detected at low concentrations in the urine.

13 NONCLINICAL TOXICOLOGY

13.1 Carcinogenesis, Mutagenesis, Impairment of Fertility

Olopatadine administered orally was not carcinogenic in mice and rats in doses up to 500 mg/kg/day and 200 mg/kg/day, respectively. Based on a 40 μL drop size and a 50 kg person, these doses were approximately 150,000 and 50,000 times higher than the maximum recommended ocular human dose (MROHD). No mutagenic potential was observed when olopatadine was tested in an in vitro bacterial reverse mutation (Ames) test, an in vitro mammalian chromosome aberration assay or an in vivo mouse micronucleus test. Olopatadine administered to male and female rats at oral doses of approximately 100,000 times MROHD level resulted in a slight decrease in the fertility index and reduced implantation rate; no effects on reproductive function were observed at doses of approximately 15,000 times the MROHD level.

14 CLINICAL STUDIES

Results from clinical studies of up to 12 weeks duration demonstrate that Olopatadine Hydrochloride Ophthalmic Solution USP, 0.2% when dosed once a day is effective in the treatment of ocular itching associated with allergic conjunctivitis.

16 HOW SUPPLIED/STORAGE AND HANDLING

Olopatadine Hydrochloride Ophthalmic Solution USP, 0.2% is supplied in a 10 mL white, low density polyethylene (LDPE) bottle with a dropper tip, and a white polypropylene cap in the following size:

NDC 17478-305-12 2.5 mL in 10 mL bottle

STORAGE:

Store at 4° to 25°C (39° to 77°F).

17 PATIENT COUNSELING INFORMATION

17.1 Topical Ophthalmic Use Only

For topical ophthalmic administration only.

17.2 Sterility of Dropper Tip

Patients should be advised to not touch dropper tip to any surface, as this may contaminate the contents.

17.3 Concomitant Use of Contact Lenses

Patients should be advised not to wear a contact lens if their eyes are red. Patients should be advised that Olopatadine Hydrochloride Ophthalmic Solution USP, 0.2% should not be used to treat contact lens-related irritation. Patients should also be advised to remove contact lenses prior to instillation of Olopatadine Hydrochloride Ophthalmic Solution USP, 0.2%. The preservative in Olopatadine Hydrochloride Ophthalmic Solution USP, 0.2% benzalkonium chloride may be absorbed by soft contact lenses. Lenses may be reinserted following administration of Olopatadine Hydrochloride Ophthalmic Solution USP, 0.2%.

Rx only

AKORN

Manufactured by: Akorn, Inc.
Lake Forest, IL 60045

OLP00N Rev. 12/17

Principal Display Panel Text for Container Label:

NDC 17478-305-12

Olopatadine HCl

Ophthalmic Solution, USP

0.2%

(Once a day)

FOR USE IN THE EYES ONLY

Rx only 2.5 mL

Principal Display Panel Text for Carton Label:

NDC 17478-305-12

Olopatadine

HCl

Ophthalmic

Solution, USP

0.2%

(Once a day)

FOR USE IN THE EYES

ONLY

2.5 mL

Rx only Akorn Logo